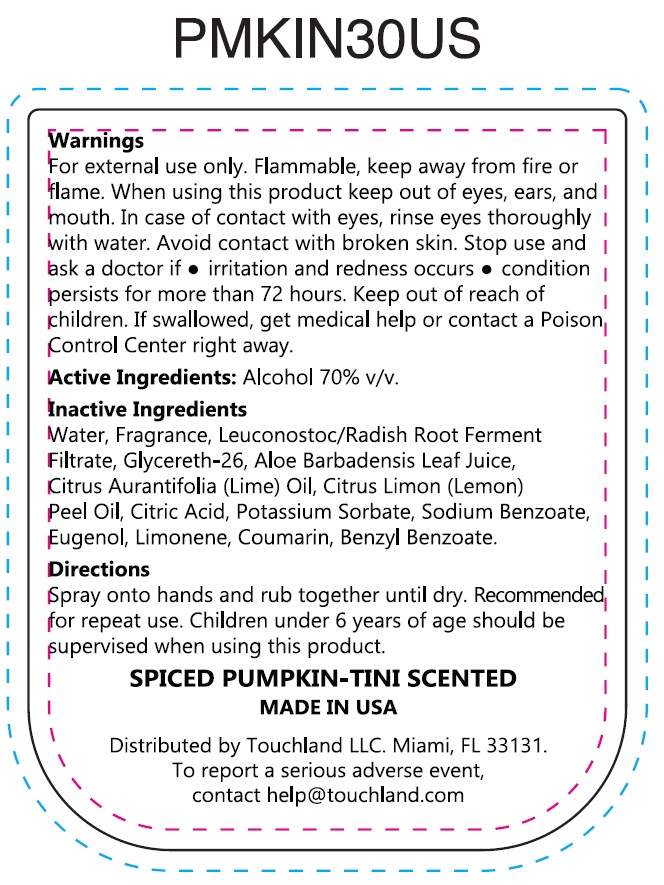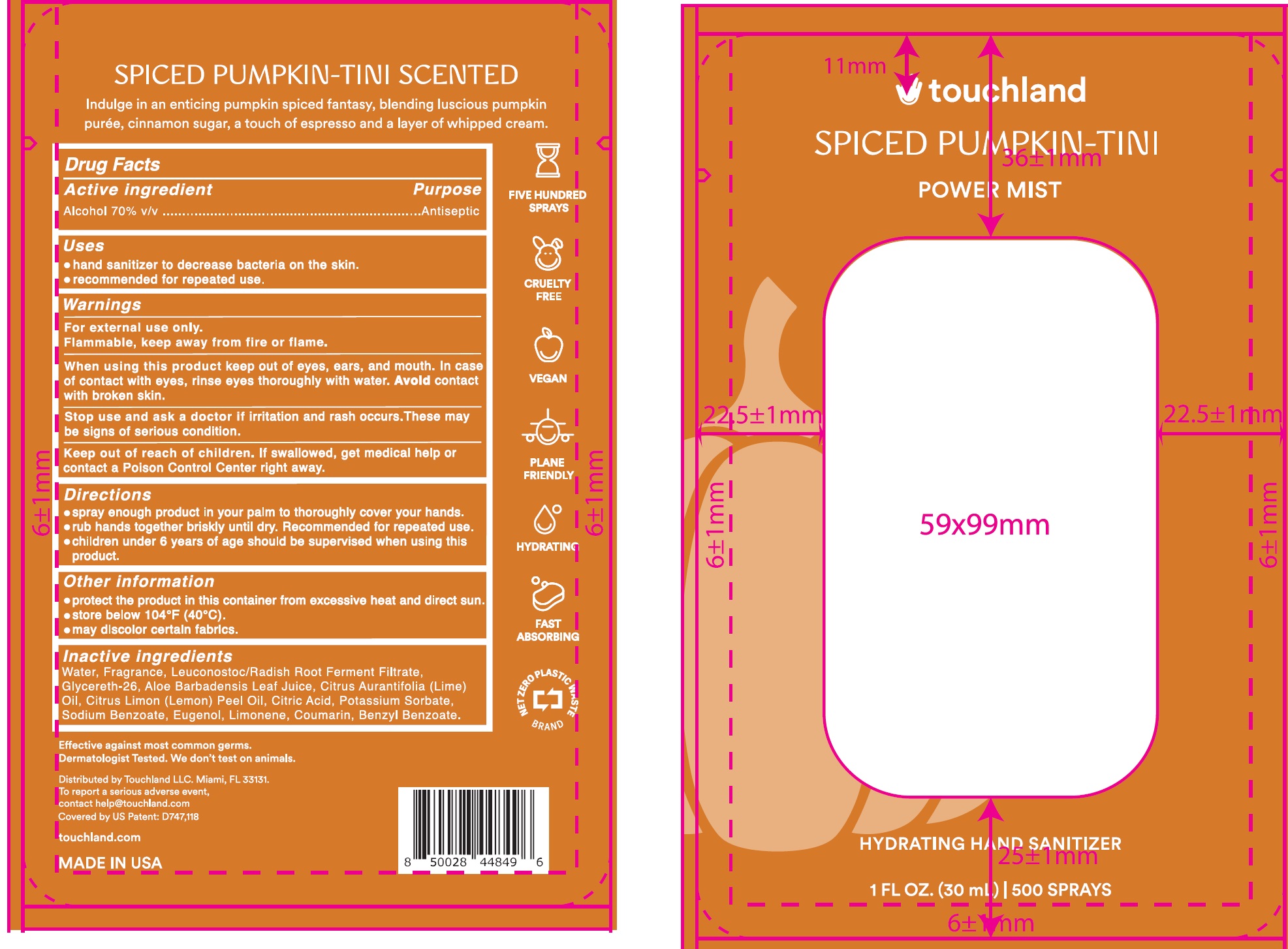 DRUG LABEL: Touchland Power Mist Spiced Pumpkin tini Scented Hydrating Hand sanitizer
NDC: 72033-142 | Form: SPRAY
Manufacturer: TOUCHLAND LLC
Category: otc | Type: HUMAN OTC DRUG LABEL
Date: 20240701

ACTIVE INGREDIENTS: ALCOHOL 70 mL/100 mL
INACTIVE INGREDIENTS: WATER; LEUCONOSTOC/RADISH ROOT FERMENT FILTRATE; GLYCERETH-26; ALOE VERA LEAF; LIME OIL, COLD PRESSED; LEMON OIL, COLD PRESSED; CITRIC ACID MONOHYDRATE; POTASSIUM SORBATE; SODIUM BENZOATE; EUGENOL; LIMONENE, (+)-; COUMARIN; BENZYL BENZOATE

Touchland Power Mist Spiced Pumpkin tini Scented Hydrating Hand sanitizer

Active ingredient

Alcohol 70% v/v

Purpose

Antiseptic

Uses

- hand sanitizer to decrease bacteria on the skin.
- recommended for repeated use.

Warnings

For external use only.

Flammable, keep away from fire or flame.

When using this product

keep out of eyes, ears, and mouth. In case of contact with eyes, rinse eyes thoroughly with water. Avoid contact with broken skin.

Stop use and ask a doctor if

irritation and rash occurs. These may be signs of serious condition.

Keep out of reach of children.

If swallowed, get medical help or contact a Poison Control Center right away.

Directions

- spray enough product in your palm to thoroughly cover your hands.
- rub hands together briskly until dry. Recommended for repeated use.
- children umder 6 years of age should be supervised when using this product.

Other information

- protect the product in this container from excessive heat and direct sun.
- store below 104°F (40°C).
- may discolor certain fabrics.

Inactive ingredients

Water, Fragrance, Leuconostoc/Radish Root Ferment Filtrate, Glycereth-26, Aloe Barbadensis Leaf Juice, Citrus Aurantifolia (Lime) Oil, Citrus Limon (Lemon) Peel Oil, Citric Acid, Potassium Sorbate, Sodium Benzoate, Eugenol, Limonene, Coumarin, Benzyl Benzoate.